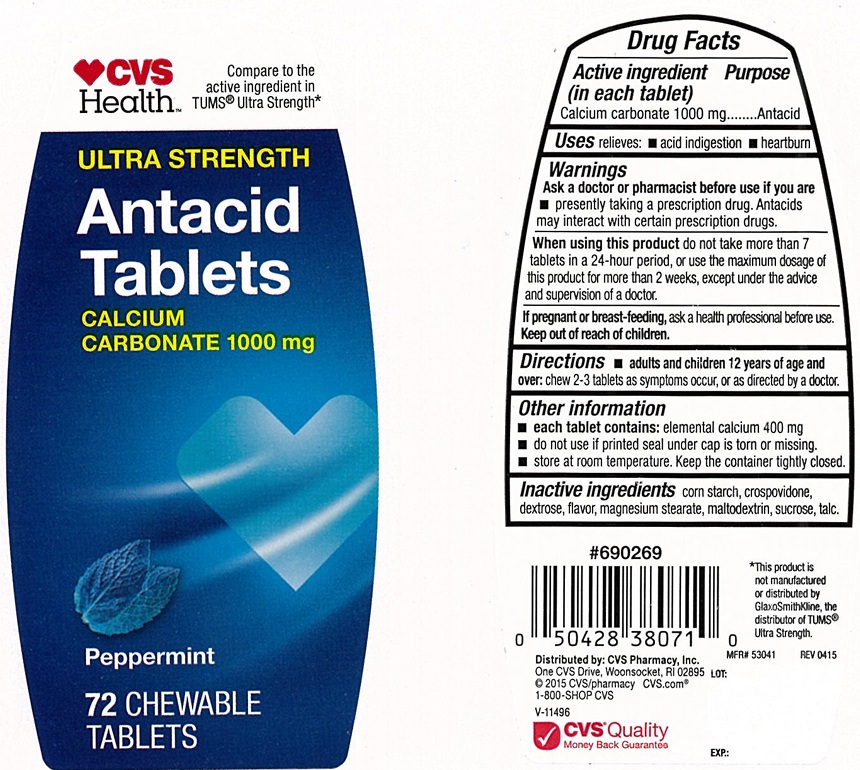 DRUG LABEL: Ultra Strength Antacid
NDC: 51316-171 | Form: TABLET, CHEWABLE
Manufacturer: CVS
Category: otc | Type: Human OTC Drug Label
Date: 20250127

ACTIVE INGREDIENTS: CALCIUM CARBONATE 1000 mg/1 1
INACTIVE INGREDIENTS: STARCH, CORN; CROSPOVIDONE, UNSPECIFIED; DEXTROSE, UNSPECIFIED FORM; MAGNESIUM STEARATE; MALTODEXTRIN; SUCROSE; TALC

Ultra Strength Peppermint Antacid 171PPT

ACTIVE INGREDIENT (in each tablet)

Calcium carbonate 1000 mg

PURPOSE

Antacid

USE(S)

relieves:

- acid indigestion
- heartburn

WARNINGS

.

ASK A DOCTOR OR PHARMACIST BEFORE USE IF YOU ARE

- presently taking a prescription drug. Antacids may interact with certain prescription drugs.

WHEN USING THIS PRODUCT

do not take more than 7 tablets in a 24-hour period, or use the maximum dosage of this product for more than 2 weeks, except under the advice and supervision of a doctor.

IF PREGNANT OR/BREASTFEEDING,

ask a health professional before use.

KEEP OUT OF REACH OF CHILDREN

.

DIRECTIONS

- adults and children 12 years of age and over: chew 2-3 tablets as symptoms occur, or as directed by a doctor.

OTHER INFORMATION

- each tablet contains: elemental calcium 400 mg
- do not use if printed seal under cap is torn or missing
- store at room temperature. keep the container tightly closed.

INACTIVE INGREDIENTS

corn starch, crospovidone, dextrose, flavors, magnesium stearate, maltodextrin, sucrose, talc.

PRINCIPAL DISPLAY PANEL

CVS Health

Compare to the active ingredient in TUMS® Ultra Strength*

ULTRA STRENGTH
Antacid

Tablets
calcium carbonate1000 mg

Peppermint flavor

72 CHEWABLE TABLETS